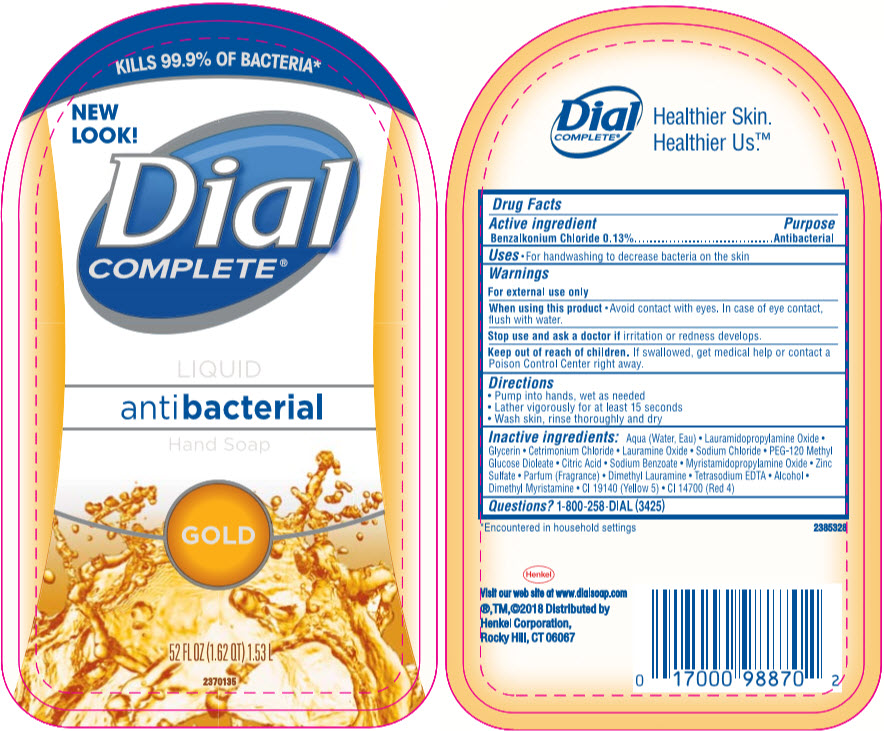 DRUG LABEL: Dial Complete Antibacterial Liquid Hand 
NDC: 69560-345 | Form: SOLUTION
Manufacturer: MID-CONTINENT PACKAGING, INC.
Category: otc | Type: HUMAN OTC DRUG LABEL
Date: 20210426

ACTIVE INGREDIENTS: Benzalkonium Chloride 1.3 mg/1 mL
INACTIVE INGREDIENTS: Water; Lauramidopropylamine Oxide; Lauramine Oxide; Cetrimonium Chloride; GLYCERIN; Sodium Chloride; PEG-120 METHYL GLUCOSE DIOLEATE; CITRIC ACID MONOHYDRATE; Sodium Benzoate; Edetate Sodium; Myristamidopropylamine Oxide; Zinc Sulfate Heptahydrate; Dimethyl Lauramine; Alcohol; Dimethyl Myristamine; FD&C YELLOW NO. 5; FD&C RED NO. 4

Dial Complete® Antibacterial Liquid Hand Soap
Gold

Drug Facts

Active ingredient

Benzalkonium Chloride 0.13%

Purpose

Antibacterial

Uses

- For handwashing to decrease bacteria on the skin.

Warnings

For external use only

When using this product

- Avoid contact with eyes. In case of eye contact, flush with water.

Stop use and ask a doctor if irritation or redness develops.

Keep out of reach of children. If swallowed, get medical help or contact a Poison Control Center right away.

Directions

- Pump into hands, wet as needed
- Lather vigorously for at least 15 seconds
- Wash skin, rinse thoroughly and dry

Inactive ingredients

Aqua (Water, Eau) • Lauramidopropylamine Oxide • Glycerin • Cetrimonium Chloride • Lauramine Oxide • Sodium Chloride • PEG-120 Methyl Glucose Dioleate • Citric Acid • Sodium Benzoate • Myristamidopropylamine Oxide • Zinc Sulfate • Parfum (Fragrance) • Dimethyl Lauramine • Tetrasodium EDTA • Alcohol • Dimethyl Myristamine • CI 19140 (Yellow 5) • CI 14700 (Red 4)

Questions?

1-800-258-DIAL (3425)

Distributed by
Henkel Corporation,
Rocky Hill, CT 06067

PRINCIPAL DISPLAY PANEL - 1.53 L Bottle Label

KILLS 99.9% OF BACTERIA*

NEW
LOOK!

Dial
COMPLETE®

LIQUID
antibacterial
Hand Soap

GOLD

52 FL OZ (1.62 QT) 1.53 L

2370135